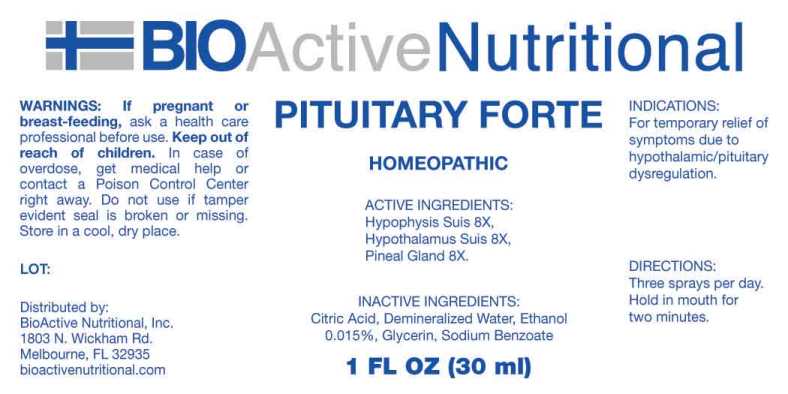 DRUG LABEL: Pituitary Forte
NDC: 43857-0006 | Form: SPRAY
Manufacturer: BioActive Nutritional, Inc.
Category: homeopathic | Type: HUMAN OTC DRUG LABEL
Date: 20250519

ACTIVE INGREDIENTS: SUS SCROFA HYPOTHALAMUS 8 [hp_X]/1 mL; SUS SCROFA PINEAL GLAND 8 [hp_X]/1 mL; SUS SCROFA PITUITARY GLAND, POSTERIOR 8 [hp_X]/1 mL
INACTIVE INGREDIENTS: CITRIC ACID MONOHYDRATE; GLYCERIN; SODIUM BENZOATE; WATER; ALCOHOL

DRUG FACTS:

ACTIVE INGREDIENTS:

Hypophysis Suis 8X, Hypothalamus (Suis) 8X, Pineal Gland (Suis) 8X.

INDICATIONS:

For temporary relief of symptoms due to hypothalamic/pituitary dysregulation.

WARNINGS:

If pregnant or breast-feeding, ask a health care professional before use.

Keep out of reach of children. In case of overdose, get medical help or contact a Poison Control Center right away.

Do not use if tamper evident seal is broken or missing.

Store in a cool, dry place.

KEEP OUT OF REACH OF CHILDREN:

In case of overdose, get medical help or contact a Poison Control Center right away.

DIRECTIONS:

Three sprays per day. Hold in mouth for two minutes.

INDICATIONS:

For temporary relief of symptoms due to hypothalamic/pituitary dysregulation.

INACTIVE INGREDIENTS:

Citric Acid, Demineralized Water, Ethanol 0.015%, Glycerin, Sodium Benzoate

QUESTIONS:

Distributed by:

BioActive Nutritional, Inc.

1803 N. Wickham Rd.

Melbourne, FL 32935

bioactivenutritional.com

PACKAGE LABEL DISPLAY:

BIOActive Nutritional

PITUITARY FORTE

HOMEOPATHIC

1 FL OZ (30 ml)